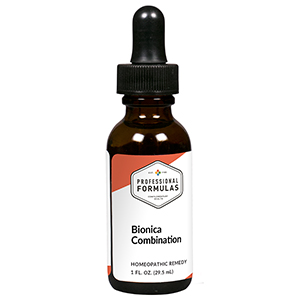 DRUG LABEL: Bionica  Combination
NDC: 63083-9280 | Form: LIQUID
Manufacturer: Professional Complementary Health Formulas
Category: homeopathic | Type: HUMAN OTC DRUG LABEL
Date: 20190815

ACTIVE INGREDIENTS: HOLOTHURIA SEA CUCUMBER 1 [hp_X]/29.5 mL; ARNICA MONTANA WHOLE 3 [hp_X]/29.5 mL; BENZOIC ACID 3 [hp_X]/29.5 mL; ECHINACEA ANGUSTIFOLIA WHOLE 3 [hp_X]/29.5 mL; MERCURIALIS PERENNIS WHOLE 3 [hp_X]/29.5 mL; APIS MELLIFERA 4 [hp_X]/29.5 mL; BAPTISIA TINCTORIA WHOLE 4 [hp_X]/29.5 mL; BRYONIA ALBA ROOT 4 [hp_X]/29.5 mL; COLCHICUM AUTUMNALE BULB 4 [hp_X]/29.5 mL; SOLANUM DULCAMARA WHOLE 4 [hp_X]/29.5 mL; EUCALYPTUS GLOBULUS LEAF 4 [hp_X]/29.5 mL; SOLANUM NIGRUM TOP 4 [hp_X]/29.5 mL; EUPATORIUM PERFOLIATUM FLOWERING TOP 6 [hp_X]/29.5 mL; TOXICODENDRON PUBESCENS LEAF 6 [hp_X]/29.5 mL
INACTIVE INGREDIENTS: ALCOHOL; WATER

R280

ACTIVE INGREDIENTS

Beche de mer 1X
Arnica montana 3X
Benzoicum acidum 3X
Echinacea angustifolia 3X
Mercurialis perennis 3X
Apis mellifica 4X
Baptisia tinctoria 4X
Bryonia 4X
Colchicum autumnale 4X
Dulcamara 4X
Eucalyptus globulus 4X
Solanum nigrum 4X
Eupatorium perfoliatum 6X
Rhus toxicodendron 6X

QUESTIONS

Professional Formulas

PO Box 2034 Lake Oswego, OR 97035

INDICATIONS

For the temporary relief of minor aches, pains, or swelling in muscles or joints.*

PURPOSE

*Claims based on traditional homeopathic practice, not accepted medical evidence. Not FDA evaluated.

WARNINGS

In case of overdose, get medical help or contact a poison control center right away.

Keep out of the reach of children.

PREGNANCY OR BREAST FEEDING

If pregnant or breastfeeding, ask a healthcare professional before use.

DIRECTIONS

Place drops under tongue 30 minutes before/after meals. Adults and children 12 years and over: Take 10 drops up to 3 times per day. Consult a physician for use in children under 12 years of age.

OTHER INFORMATION

Tamper resistant. If seal is broken, do not use. After opening, close container tightly and store at room temperature away from heat.

INACTIVE INGREDIENTS

40% ethanol, purified water.

LABEL

Est 1985

Professional Formulas

Complementary Health

Bionica Combination

Homeopathic Remedy

1 FL. OZ. (29.5 mL)